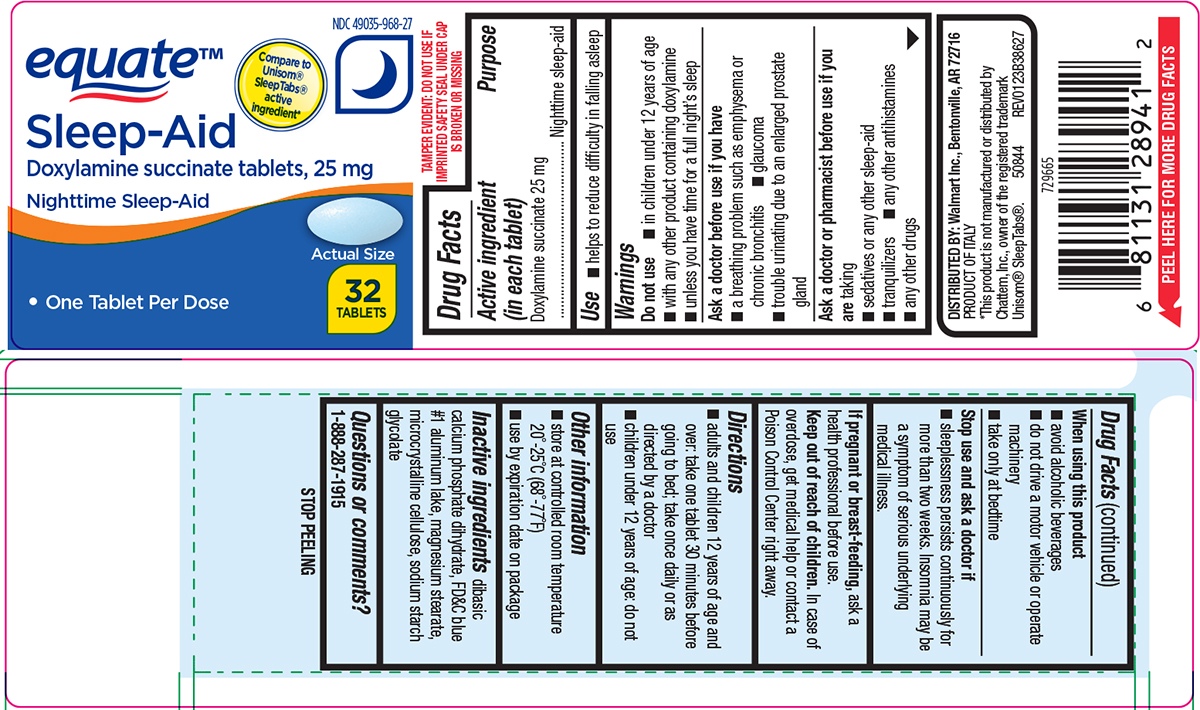 DRUG LABEL: Sleep Aid
NDC: 49035-968 | Form: TABLET
Manufacturer: Wal-Mart Stores Inc
Category: otc | Type: HUMAN OTC DRUG LABEL
Date: 20250510

ACTIVE INGREDIENTS: DOXYLAMINE SUCCINATE 25 mg/1 1
INACTIVE INGREDIENTS: DIBASIC CALCIUM PHOSPHATE DIHYDRATE; FD&C BLUE NO. 1 ALUMINUM LAKE; MAGNESIUM STEARATE; MICROCRYSTALLINE CELLULOSE; SODIUM STARCH GLYCOLATE TYPE A POTATO

Equate 44-386

Active ingredient (in each tablet)

Doxylamine succinate 25 mg

Purpose

Nighttime sleep-aid

Use

- helps to reduce difficulty in falling asleep

Warnings

Do not use

- in children under 12 years of age
- with any other product containing doxylamine
- unless you have time for a full night’s sleep

Ask a doctor before use if you have

- glaucoma
- a breathing problem such as asthma, emphysema or chronic bronchitis
- difficulty in urination due to enlargement of the prostate gland

Ask a doctor or pharmacist before use if you are

taking

- sedatives or any other sleep-aid
- tranquilizers
- any other antihistamines
- any other drugs

When using this product

- avoid alcoholic beverages
- do not drive a motor vehicle or operate machinery
- take only at bedtime

Stop use and ask a doctor if

- sleeplessness persists continuously for more than two weeks. Insomnia may be a symptom of serious underlying medical illness.

If pregnant or breast-feeding,

ask a health professional before use.

Keep out of reach of children.

In case of overdose, get medical help or contact a Poison Control Center right away.

Directions

- adults and children 12 years of age and over: take one tablet 30 minutes before going to bed; take once daily or as directed by a doctor
- children under 12 years of age: do not use

Other information

- store at controlled room temperature 20°-25°C (68°-77°F)
- use by expiration date on package

Inactive ingredients

dibasic calcium phosphate dihydrate, FD&C blue #1 aluminum lake, magnesium stearate, microcrystalline cellulose, sodium starch glycolate

Questions or comments?

1-888-287-1915

Principal display panel

equate™

NDC 49035-968-27

Compare to
Unisom®
SleepTabs®
active
ingredient*

Sleep-Aid
Doxylamine succinate 25 mg
Nighttime Sleep-Aid

• One Tablet Per Dose

Actual Size

32
TABLETS

TAMPER EVIDENT: DO NOT USE IF
IMPRINTED SAFETY SEAL UNDER CAP
IS BROKEN OR MISSING

DISTRIBUTED BY: Walmart Inc., Bentonville, AR 72716
PRODUCT OF ITALY

*This product is not manufactured or distributed by
Chattem, Inc., owner of the registered trademark
Unisom® SleepTabs®. 50844 REV0123B38627

Equate 44-386